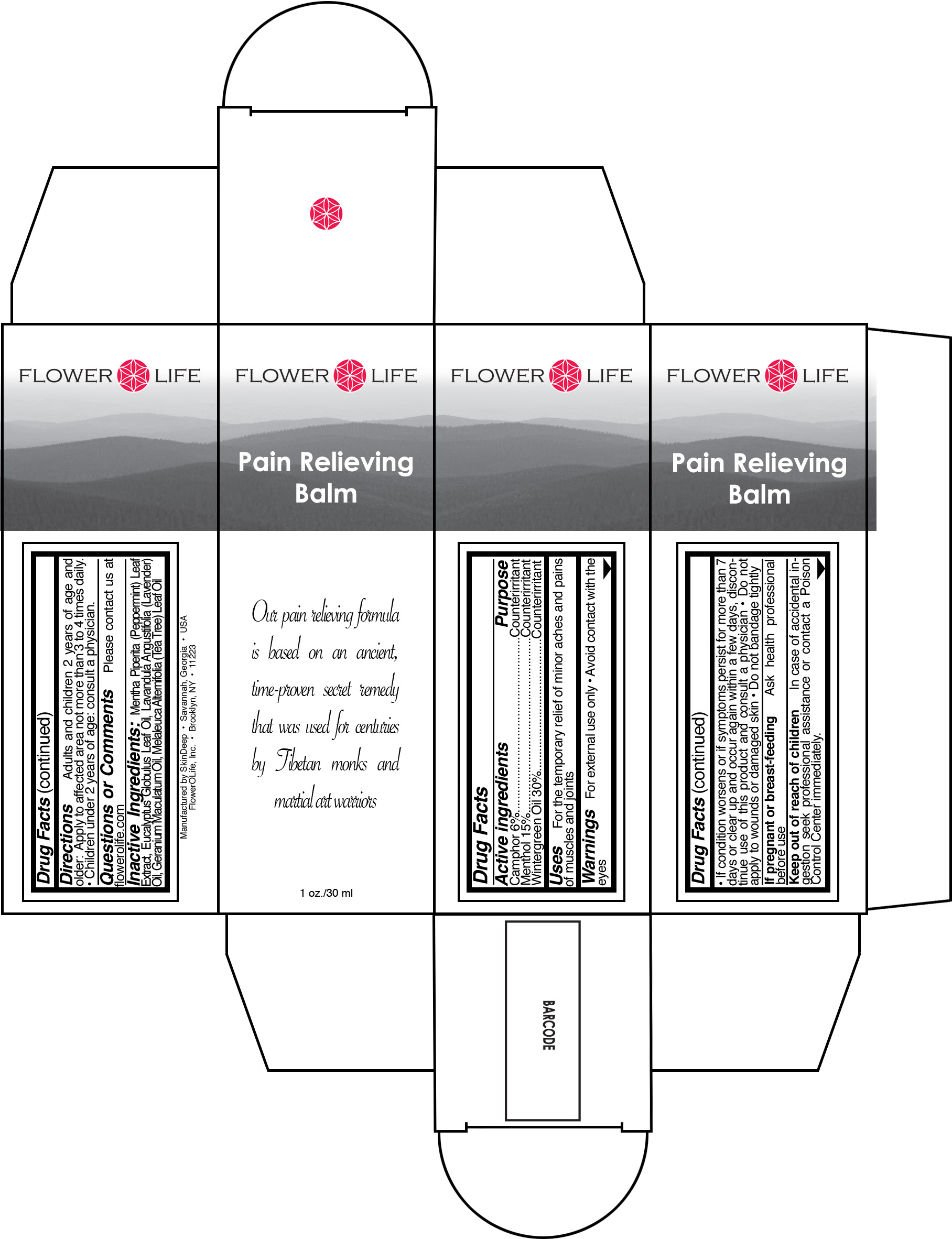 DRUG LABEL: Flower O Life
NDC: 45156-2250 | Form: OIL
Manufacturer: Skin Deep
Category: otc | Type: HUMAN OTC DRUG LABEL
Date: 20110808

ACTIVE INGREDIENTS: Camphor (Natural) 6 g/100 g; Menthol 15 g/100 g; Methyl Salicylate 30 g/100 g
INACTIVE INGREDIENTS: Peppermint; Corymbia Citriodora Leaf Oil; Lavender Oil; Geranium Maculatum Root; Tea Tree Oil

Drug Facts

Active Ingredient

Camphor (6.0%)

Menthol (15.0%)

Wintergreen Oil (30.0%)

Purpose

Counterirritant

Counterirritant

Counterirritant

Uses

For the temporary relief of minor aches and pains of muscles and joints.

Warnings

For external use only

Avoid contact with the eyes

If condition worsens or if symptoms persist for more than 7 days or clear up and occur again within a few days, discontinue use of this product and consult a physician

Do not apply to wounds or damaged skin

Do not bandage tightly

If pregnant or breast-feeding

Ask health professional before use

Keep out of reach of children

In case of accidental ingestion seek professional assistance of contact a Poison Control Center immediately.

Directions

Adults and children 2 years of age and older: Apply to affected area not more than 3 to 4 times daily.

Children under 2 years of age: Consult a physician.

Inactive Ingredients

Mentha Piperita (Peppermint) Leaf Extract, Eucalyptus Globulus Leaf Oil, Lavandula Angustifolia (Lavender) Oil, Geranium Maculatum Oil, Melaleuca Alternifolia (Tea Tree) Leaf Oil

Questions or Comments

Please contact us at www.flowerolife.com

Principal Display Panel

Flower O Life

Pain Relieving Balm

1 oz./30 mL

Manufactured by SkinDeep

Savannah, Georgia USA

FlowerOLife Inc

Brooklyn, NY 11223